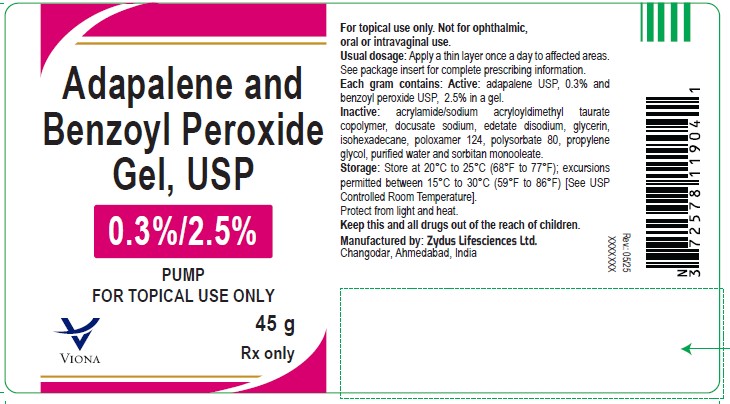 DRUG LABEL: Adapalene and benzoyl peroxide
NDC: 70771-1716 | Form: GEL
Manufacturer: Zydus Lifesciences Limited
Category: prescription | Type: HUMAN PRESCRIPTION DRUG LABEL
Date: 20250613

ACTIVE INGREDIENTS: ADAPALENE 3 mg/1 g; BENZOYL PEROXIDE 25 mg/1 g
INACTIVE INGREDIENTS: 1-PROPANESULFONIC ACID, 2-METHYL-2-((1-OXO-2-PROPEN-1-YL)AMINO)-, SODIUM SALT (1:1), POLYMER WITH 2-PROPENAMIDE; DOCUSATE SODIUM; EDETATE DISODIUM; GLYCERIN; ISOHEXADECANE; POLOXAMER 124; POLYSORBATE 80; PROPYLENE GLYCOL; SORBITAN MONOOLEATE; WATER

ADAPALENE and BENZOYL PEROXIDE gel, USP

PACKAGE LABEL.PRINCIPAL DISPLAY PANEL

Adapalene and benzoyl peroxide gel, USP 0.3%/2.5%

NDC 70771-1716-4

45 g

Rx only